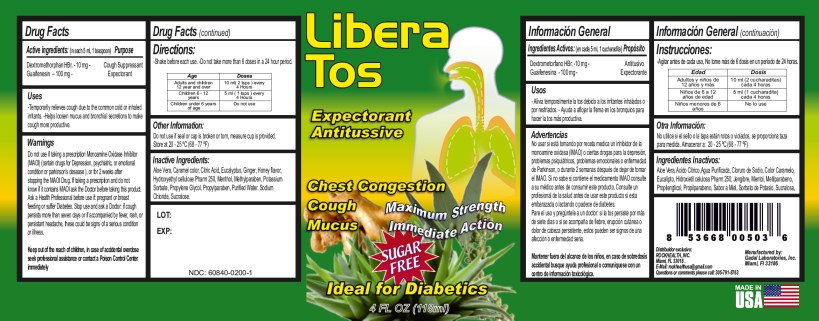 DRUG LABEL: Libera Tos
NDC: 60840-0200 | Form: LIQUID
Manufacturer: RockHealth, Inc
Category: otc | Type: HUMAN OTC DRUG LABEL
Date: 20131101

ACTIVE INGREDIENTS: DEXTROMETHORPHAN HYDROBROMIDE 10 mg/5 mL; GUAIFENESIN 100 mg/5 mL
INACTIVE INGREDIENTS: ALOE; CARAMEL; CITRIC ACID MONOHYDRATE; EUCALYPTUS OIL; GINGER; HYDROXYETHYL CELLULOSE (140 MPA.S AT 5%); MENTHOL; METHYLPARABEN; POTASSIUM SORBATE; PROPYLENE GLYCOL; PROPYLPARABEN; SODIUM CHLORIDE; SUCRALOSE; WATER

Libera Tos Diabetic

Active Ingredients:(in each teaspoonful 5 ml.) Purpose

Dextromethorphan Hydrobromide 10 mg .................................... Cough Suppressant

Guaifenesin 100 mg ................................................................... Expectorant

Uses:

- Temporarily relieves cough due to the common cold or inhaled irritants.
- Helps loosen mucus and bronchial secretions to make cough more productive.

Warnings

Do not use if taking a prescription Monoamine Oxidase Inhibitor(MAOI) (certain drugs for Depression, psychiatric, or emotional condition or parkinson’s desease), or for 2 weeks after stopping the MAOI Drug. If taking a prescription and do not know if it contains MAOI ask the Doctor before taking this product. Ask a Health Professional before use if: pregnant or breast feeding or suffer Diabetes. Stop use and ask a Doctor: if cough persists more than seven days or if accompanied by fever, rash, or persistant headache, these could be signs of a serious condition or illness.

Keep out of the reach of children, in case of accidental overdose seek professional assistance or contact a Poison Control Center immediately

Keep out of reach of children.

In case of accidental overdose, get medical help or contact a Poison Control Center right away.

Directions

Shake well immediately before each use.

Do not exceed 6 doses in any 24 hour period.

AGE | DOSES
Adults and Children 12 years and over | 10 ml (2 tsps) every 4 hours
Children 6 to under 12 years of age | 5 ml (1 tsp) every 4 hours
Children under 6 years of age | Do not use

Other Information:Do not use if seal or cap is broken or torn, measure cup is provided
Store at 20 - 25 ºC (68 - 77 ºF).

INACTIVE INGREDIENT

Inactive Ingredients:Aloe Vera, Caramel color, Citric Acid, Eucalyptus, Ginger,Honey flavor, Hydroxyethyl cellulose Pharm 250, Menthol, Methylparaben,Potassium Sorbate,Propylene Glycol, Propylparaben, Purified water,Sodium Chloride, Sucralose.

Questions or Comments?

please call: 305-791-8763

Manufactured by

Gadal Laboratories, Inc., Miami, Fl 33186

Exclusively Distributed by

ROCKHEALTH, INC., Miami, Fl 33018

Made in U.S.A.